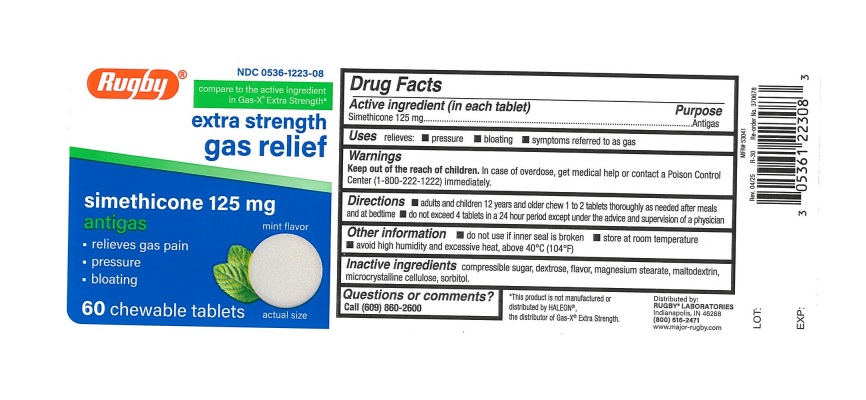 DRUG LABEL: Rugby Gas relief
NDC: 0536-1223 | Form: TABLET, CHEWABLE
Manufacturer: Rugby Laboratories
Category: otc | Type: Human OTC Drug Label
Date: 20251124

ACTIVE INGREDIENTS: DIMETHICONE 125 mg/1 1
INACTIVE INGREDIENTS: SUGARCANE; MALTODEXTRIN; DEXTROSE, UNSPECIFIED FORM; MAGNESIUM STEARATE; MICROCRYSTALLINE CELLULOSE; SORBITOL

Rugby Extra Strength Gas Relief Chewable Tablets

ACTIVE INGREDIENT(in each tablet)

Simethicone 125 mg

PURPOSE

Anti-gas

USE(S)

relieves:

- pressure
- bloating
- symptoms referred to as gas

WARNINGS

.

KEEP OUT OF REACH OF CHILDREN

Keep out of the reach of children. In case of overdose, get medical help or contact a Poison Control Center immediately.

DIRECTIONS

- chew 1 to 2 tablets thoroughly as needed after meals and at bedtime
- do not exceed 4 tablets in a 24 hour period except under the advice and supervision of a physician

OTHER INFORMATION

- do not use if inner seal is broken
- store at room temperature
- avoid high humidity and excessive heat, above 40oC (104oF)

INACTIVE INGREDIENTS

compressible sugar, dextrose, flavor, magnesium stearate, maltodextrin, microcrystalline cellulose, sorbitol.

QUESTIONS OR COMMENTS?

1 (800) 645-2158

PRINCIPAL DISPLAY PANEL

NDC 0536-1223-08

compare to active ingredient in gas-x® Extra strength*
Rugby
extra strength
gas relief
Simethicone 125 mg each
antigas mint flavor

- relieves gas pain
- pressure
- boating

60 CHEWABLE TABLETS